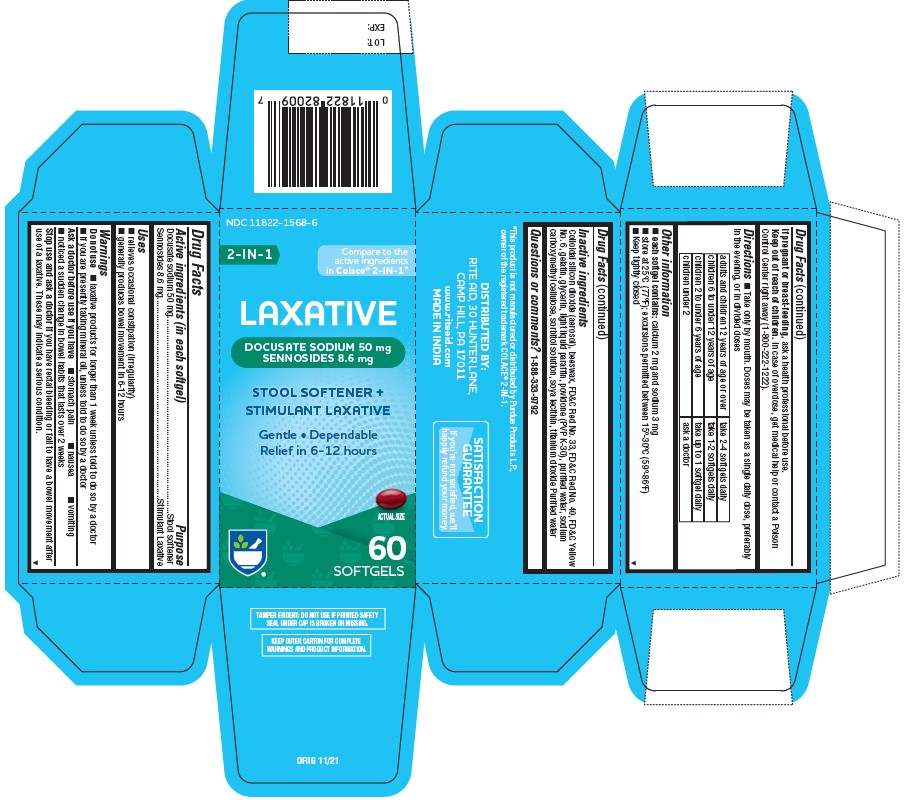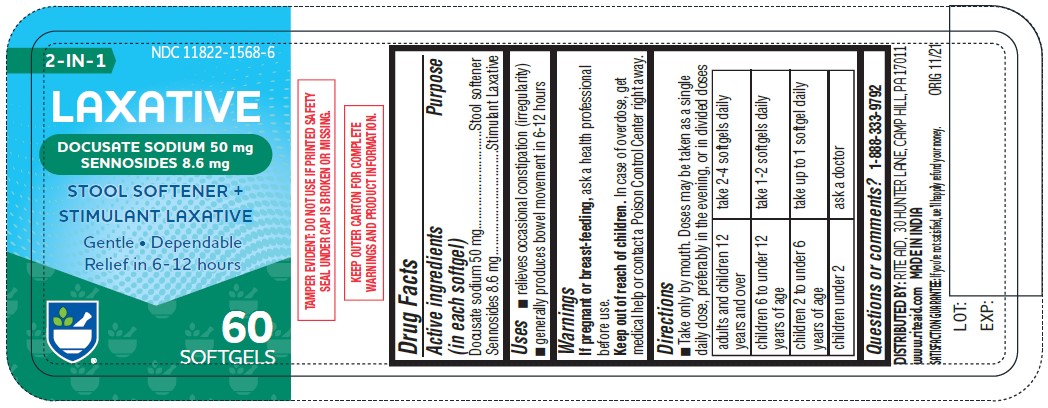 DRUG LABEL: LAXATIVE
NDC: 11822-1572 | Form: CAPSULE, LIQUID FILLED
Manufacturer: RITE AID CORPORATION
Category: otc | Type: HUMAN OTC DRUG LABEL
Date: 20241230

ACTIVE INGREDIENTS: DOCUSATE SODIUM 50 mg/1 1; SENNOSIDES 8.6 mg/1 1
INACTIVE INGREDIENTS: PARAFFIN; LECITHIN, SOYBEAN; SYNTHETIC BEESWAX; SILICON DIOXIDE; CARBOXYMETHYLCELLULOSE SODIUM; TITANIUM DIOXIDE; GELATIN; GLYCERIN; NONCRYSTALLIZING SORBITOL SOLUTION; POVIDONE K30; FD&C YELLOW NO. 6; D&C RED NO. 33; FD&C RED NO. 40; WATER

LAXATIVE

Active Ingredient (in each Softgel)

Docusate sodium 50 mg

Sennosides 8.6 mg

Purpose

Stool softener

Laxative

Uses

• relieves occasional constipation (irregularity) • generally produces bowel movement in 6–12 hours

Warnings

Do not use • if you are now taking mineral oil, unless directed by a doctor • laxative products for longer than 1 week, unless directed by a doctor

Ask a doctor before use if you have • stomach pain • nausea • vomiting • noticed a sudden change in bowel habits that continues over a period of 2 weeks

Ask a doctor or pharmacist before use if you have rectal bleeding or fail to have a bowel movement after use of a laxative. These may indicate a serious condition.

Stop use and ask a doctor if • you have rectal bleeding or fail to have a bowel movement after use of a laxative. These could be signs of a serious condition • you need to use a stool softener
laxative for more than 1 week

PREGNANCY OR BREAST FEEDING

If pregnant or breast-feeding, ask a health professional before use.

Keep out of reach of children. In case of overdose, get medical help or contact a Poison Control Center right away. (1-800-222-1222)

Directions

take preferably at bedtime or as directed by a doctor

Age | Starting Dosage | Maximum Dosage
adults & children 12 years of age & over | 2 tablets once a day | 4 tablets twice a day
children 6 to under 12 years of age | 1 tablet once a day | 2 tablets twice a day
children 2 to under 6 years | ½ tablet once a day | 1 tablet twice a day
children under 2 years | ask a doctor | ask a doctor

Other information

• each tablet contains: calcium 2 mg and sodium 6 mg
• store at 25°C (77°F); excursions permitted between 15°–30°C (59°–86°F)

Inactive ingredients

Light liquid paraffin, Soya lecithin, Beeswax, Colloidal silicon dioxide (aerosol), Sodium Carboxymethyl Cellulose, titanium dioxide, Gelatin, Glycerin, Sorbitol sorbitan, Povidone, FD&C Yellow-6, FD&C Red-33, spl, Purified water

Questions or comments?

1-888-333-9792

Distributed by:
RITE AID
30 Hunter Lane, Camp Hill, PA 17011
www.riteaid.com
Made in India